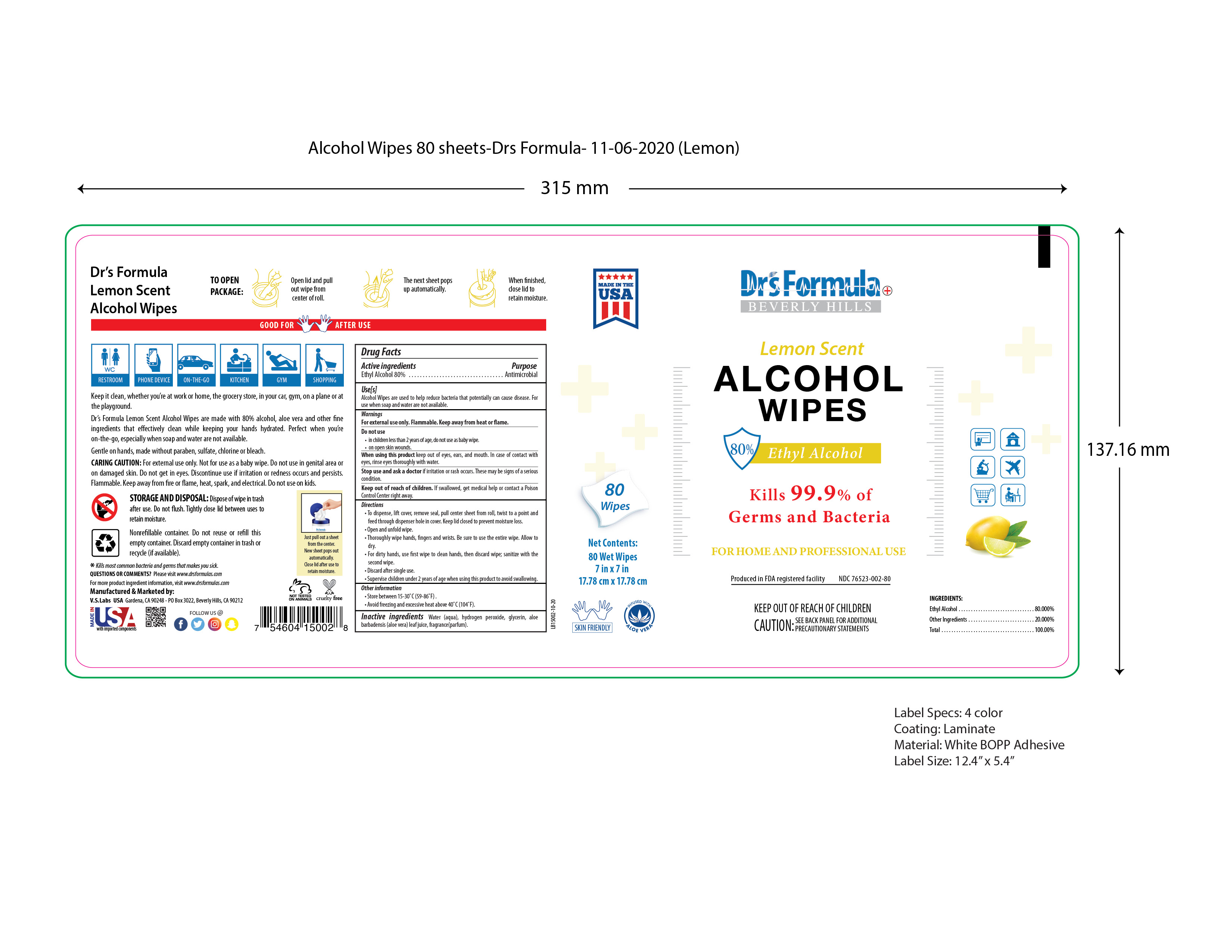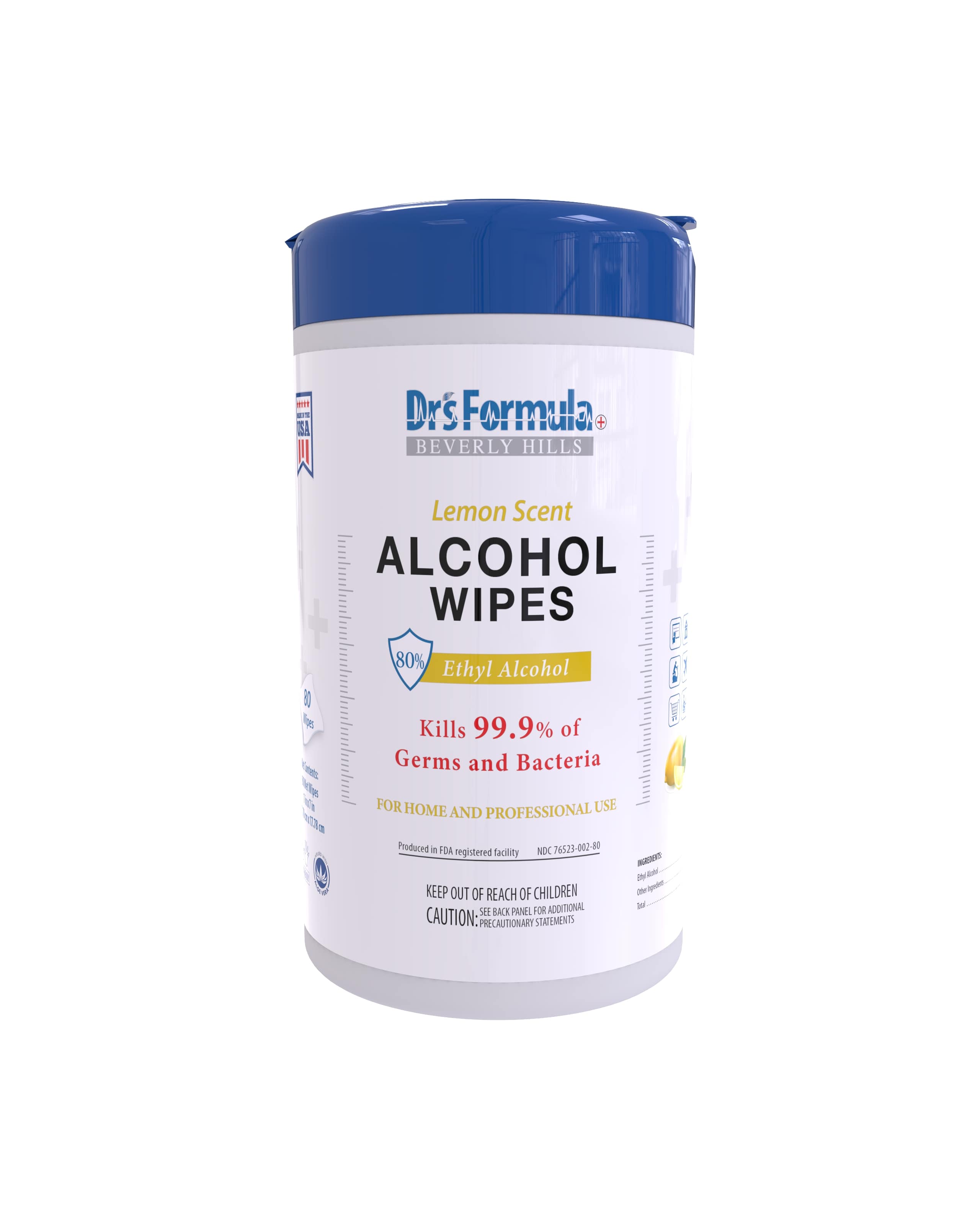 DRUG LABEL: Alcohol Wipes Lemon Scent
NDC: 76523-002 | Form: CLOTH
Manufacturer: Valley of the Sun Cosmetics LLC
Category: otc | Type: HUMAN OTC DRUG LABEL
Date: 20201114

ACTIVE INGREDIENTS: ALCOHOL 80 mL/100 mL
INACTIVE INGREDIENTS: GLYCERIN 1.45 mL/100 mL; ALOE VERA LEAF 0.3 mL/100 mL; HYDROGEN PEROXIDE 0.125 mL/100 mL; FRAGRANCE LEMON ORC2001060 0.2 mL/100 mL; WATER 17.93 mL/100 mL

Alcohol Wipes Lemon Scent

Active Ingredients

Ethyl Alcohol 80%

Purpose

Antimicrobial

Uses

Alcohol Wipes are used to help reduce bacteria that potentially can cause disease. For use when soap and water are not available.

Warnings

For external use only. Keep away from heat or flame.

Do not use

- in children less than 2 years of age, do not use as baby wipe.
- on open skin wounds.

When using this product

Keep out of eyes, ears, and mouth. In case of contact with eyes, rinse eyes thoroughly with water.

Stop use and ask a doctor

If irritation or rash occurs. These may be signs of a serious condition.

Keep out of reach of children

If swallowed, get medical help or contact a poison control center right away.

Directions

- To dispense, lift cover, remove seal, pull center sheet from roll, twist to a point and feed through dispenser hole in cover. Keep lid closed to prevent moisture loss.
- Open and unfold wipe.
- Thoroughly wipe hands, fingers, and wrists. Be sure to use the entire wipe. Allow to dry.
- For dirty hands, use first wipe to clean hands, then discard wipe; sanitize with the second wipe.
- Discard after single use.
- Supervise children under 2 years of age when using this product to avoid swallowing.

Other information

- Store between 15-30ºC (59-86°F)
- Avoid freezing and excessive heat above 40ºC(104°F)

Inactive ingredients

Water (aqua), hydrogen peroxide, glycerin, aloe barbadensis (aloe vera) leaf juice, lemon fragrance (parfum)

Package Label

Alcohol Wipes Lemon Scent, 80 wipes, 454ml, NDC: 76523-002-80